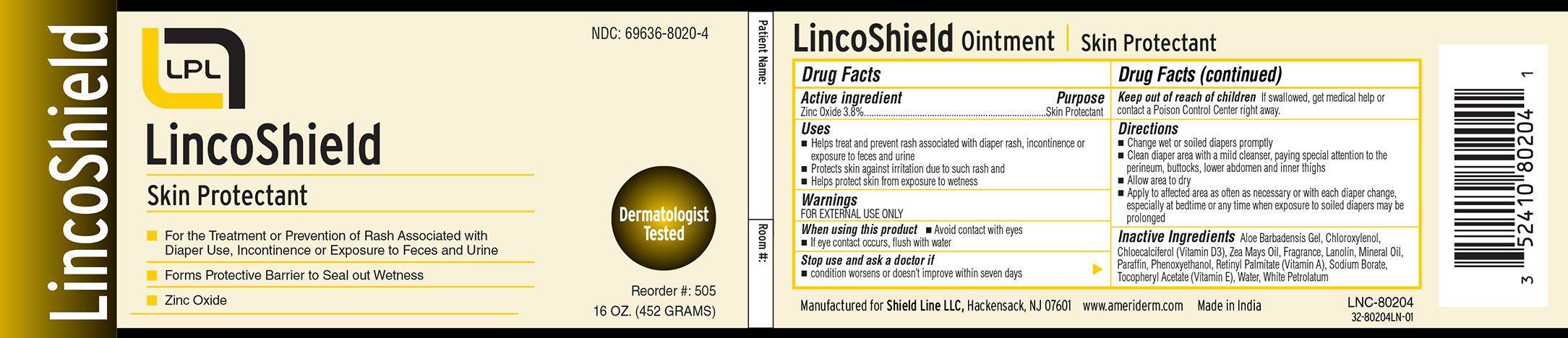 DRUG LABEL: LincoShield
NDC: 69636-8020 | Form: OINTMENT
Manufacturer: Lincoln Pharmaceuticals Ltd.
Category: otc | Type: HUMAN OTC DRUG LABEL
Date: 20161005

ACTIVE INGREDIENTS: ZINC OXIDE 3.8 g/100 g
INACTIVE INGREDIENTS: CORN OIL; SODIUM BORATE; ALPHA-TOCOPHEROL; ALOE VERA LEAF; CHLOROXYLENOL; CHOLECALCIFEROL; LANOLIN; MINERAL OIL; PARAFFIN; PHENOXYETHANOL; VITAMIN A PALMITATE; WATER; PETROLATUM

Active Ingredient

Zinc Oxide 3.8%

Purpose

Skin Protectant

Uses

- Helps treat and prevent diaper rash, incontinence or exposure to feces and urine
- Protects skin against irritation due to such rash
- Helps protect skin from exposure to wetness

Warnings

FOR EXTERNAL USE ONLY

When using this product

- Avoid contact with eyes
- If eye contact occurs, flush with water

Stop use and ask a doctor if

- condition worsens or doesn't improve within seven days

Keep out of reach of children

If swallowed, get medical help or contact a Poison Control Center right away

Directions

- Change wet or soiled diapers promptly
- Clean diaper area with a mild cleanser, paying special attention to the perineum, buttocks, lower abdomen and inner thighs
- Allow area to dry
  - Apply to affected area as often as necessary or with each diaper change, especially at bedtime or any time when exposure to

soiled diapers may be prolonged

Inactive Ingredients

Aloe Barbadensis Gel, Chloroxylenol, Cholecalciferol (Vitamin D3), Zea Mays Oil, Fragrance, Lanolin, Mineral Oil, Paraffin, Phenoxyethanol, Retinyl Palmitate (Vitamin A), Sodium Borate, Tocopherol Acetate (Vitamin E), Water, White Petrolatum